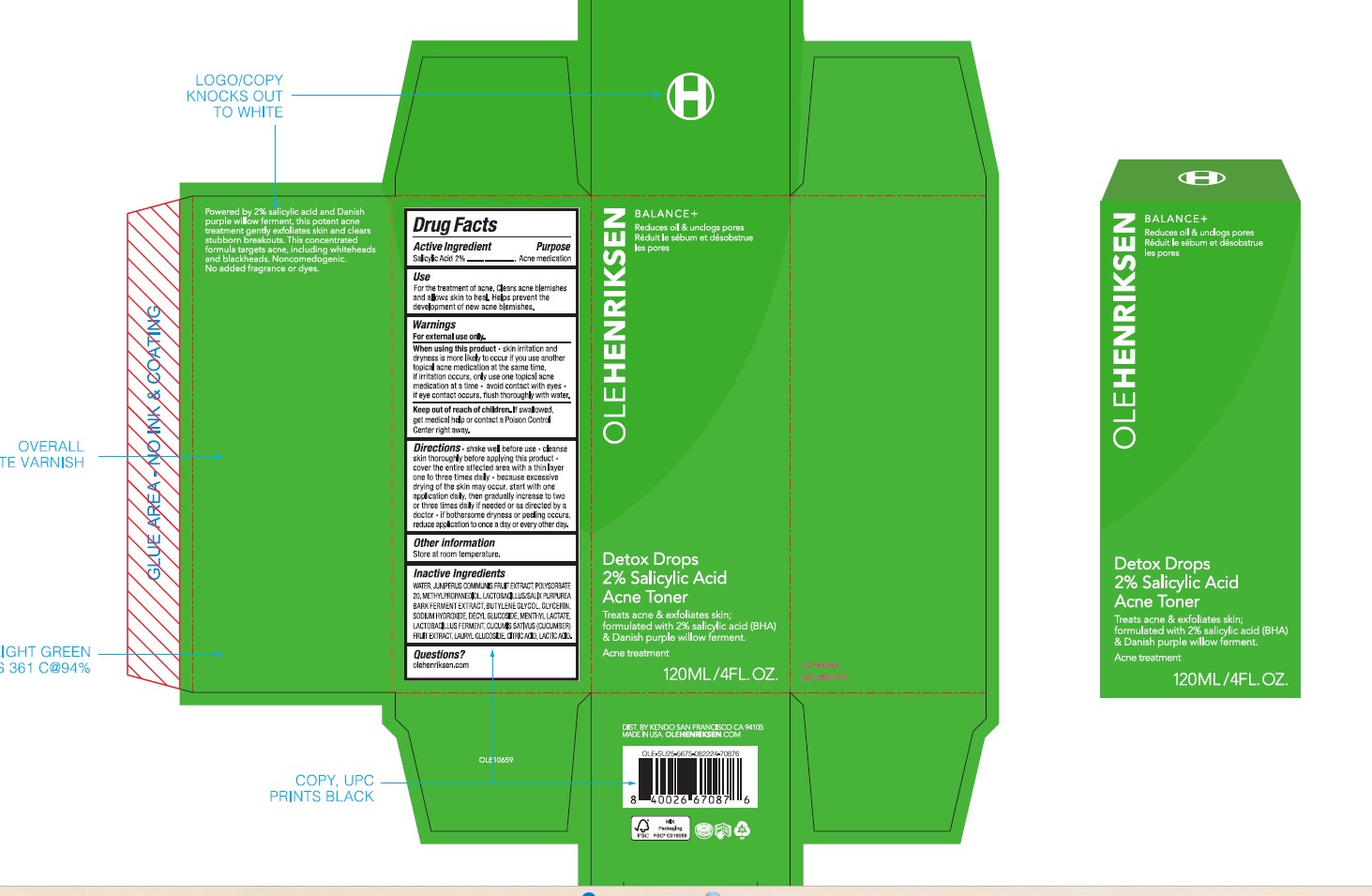 DRUG LABEL: Detox Drops 2% Salicylic Acid Acne Toner
NDC: 68577-189 | Form: LIQUID
Manufacturer: COSMAX USA, CORPORATION
Category: otc | Type: HUMAN OTC DRUG LABEL
Date: 20241219

ACTIVE INGREDIENTS: SALICYLIC ACID 2 mg/100 mg
INACTIVE INGREDIENTS: POLYSORBATE 20; CITRIC ACID; WATER; LAURYL GLUCOSIDE; GLYCERIN; CUCUMIS SATIVUS (CUCUMBER) FRUIT; LACTIC ACID; LIMOSILACTOBACILLUS FERMENTUM ME-3; METHYLPROPANEDIOL; JUNIPER BERRY; DECYL GLUCOSIDE; MENTHYL LACTATE; BUTYLENE GLYCOL; SODIUM HYDROXIDE

OLEHENRIKSEN DETOX DROPS 2% SALICYLIC ACID ACNE TONER

Active Ingredient

Salicylic Acid 2%

Purpose

Acne medication

USES

Use

For the treatment of acne. Clears acne blemishes and allows skin to heal. Helps prevent the development of new blemishes.

When using this product

- skin irritation and dryness is more likely to occur if you use another topical acne medication at the same time, if irritation occurs, only use one topical acne medication at a time
- avoid contact with eyes
- if eye contact occurs, flush thoroughly with water

Warnings

For external use only.

Keep out of reach of children. If swallowed, get medical help or contact a Poison Control Center right away.

DIRECTIONS

- shake well before use
- clean skin thoroughly before applying this product
- cover the entire affected area with a thin layer one to three times daily
- because excessive drying of the skin may occur, start with one application daily, then gradually increase to two or three times daily if needed or as directed by a doctor
- if bothersome dryness or peeling occurs, reduce application to once a day or every other day.

OTHER INFORMATION

Store at room temperature

Inactive Ingredients

WATER, JUNIPERUS COMMUNIS FRUIT EXTRACT, POLYSORBATE 20, METHYLPROPANEDIOL, LACTOBACILLUS/SALIX PURPUREA BARK FERMENT EXTRACT, BUTYLENE GLYCOL, GLYCERIN, SODIUM HYDROXIDE, DECYL GLUCOSIDE, MENTHYL LACTATE, LACTOBACILLUS FERMENT, CUCUMIS SATIVUS (CUCUMBER) FRUIT EXTRACT, LAURYL GLUCOSIDE, CITRIC ACUD, LACTIC ACID.